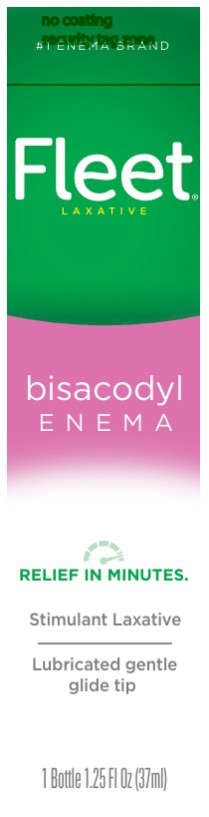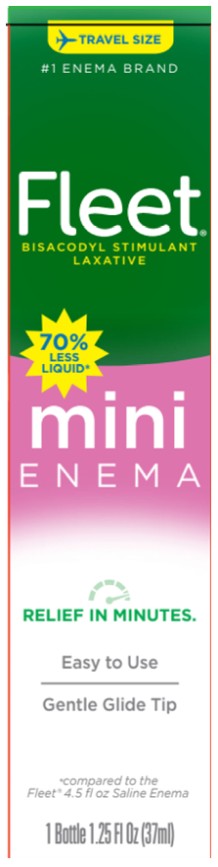 DRUG LABEL: Fleet
NDC: 0132-0703 | Form: ENEMA
Manufacturer: C.B. Fleet Company, Inc.
Category: otc | Type: HUMAN OTC DRUG LABEL
Date: 20250623

ACTIVE INGREDIENTS: BISACODYL 10 mg/30 mL
INACTIVE INGREDIENTS: CARBOMER HOMOPOLYMER TYPE B (ALLYL PENTAERYTHRITOL CROSSLINKED); GLYCERIN; METHYLPARABEN; OCTOXYNOL 9; PROPYLPARABEN; WATER; SODIUM HYDROXIDE

Fleet Bisacodyl Enema NDC 0132-0703-36

Drug Facts

Purpose

Bisacodyl 10 mg .............Stimulant laxative/ bowel cleanser

Uses

- for relief of fecal impaction
- for relief of occasional constipation
- for removal of residue after barium administration

This product usually produces a bowel movement in 5 to 20 minutes.

Warnings

For rectal use only.

Do not use

when abdominal pain, nausea, or vomiting are present unless directed by a doctor.

Ask a doctor before using this product if you

- have a sudden change in bowel habits lasting more than 2 weeks
- already used a laxative for more than 1 week

This product may cause abdominal discomfort, faintness, rectal burning, and mild cramps.

Stop use and ask a doctor if you have

• rectal bleeding

• no bowel movement within 20 minutes of using this product.

These symptoms may indicate a serious condition.

If pregnant or breast-feeding,

ask a health professional before use.

Keep out of reach of children.

If swallowed, get medical help or contact a Poison Control Center right away.

Directions

Single Daily Dosage (per 24 hours)

adults and children 12 years and over | 1 bottle per day
children under 12 years | DO NOT USE

Other information

• store at temperatures not above 86˚ F (30˚ C)

Inactive ingredients

carbomer 934P, glycerin, methylparaben, octoxynol-9, propylparaben, purified water, sodium hydroxide

Questions?

or www.fleetlabs.com

Tamper Evident: bottle sealed for safety. If bottle wrapper with fleet emblem is torn, damaged or missing, do not use.

PRINCIPAL DISPLAY PANEL

Fleet
Laxative
bisacodyl
Enema